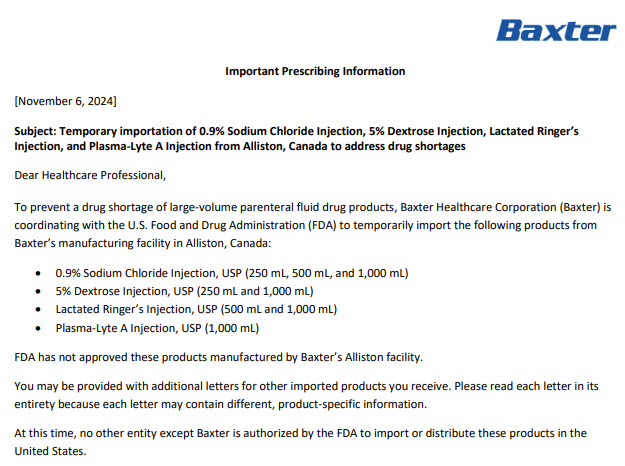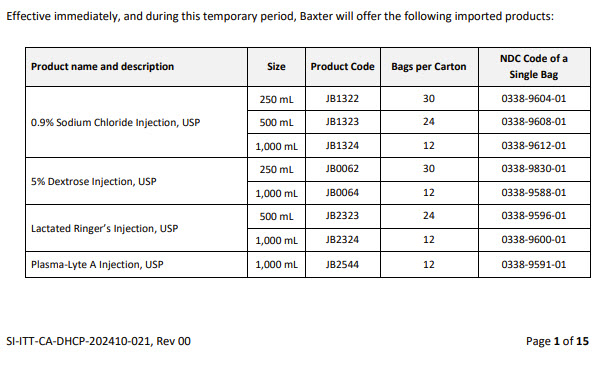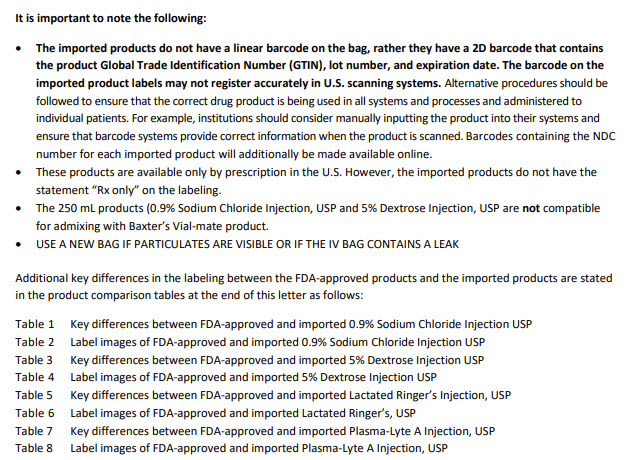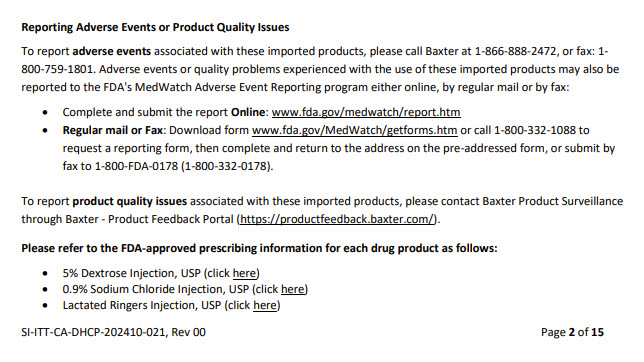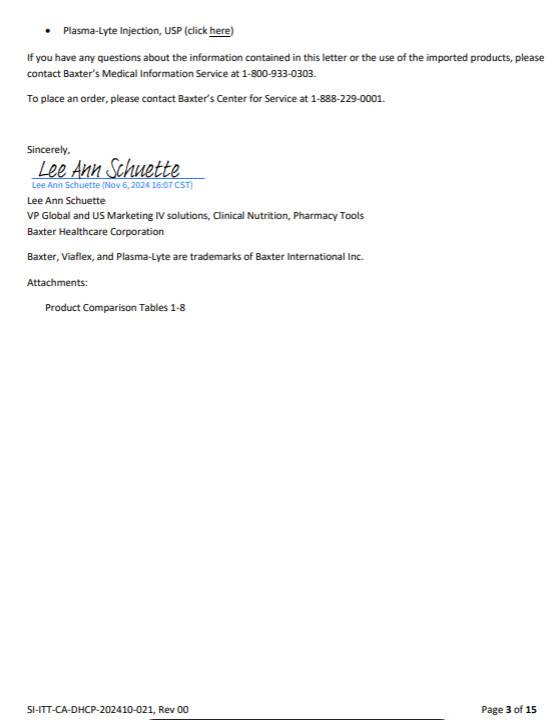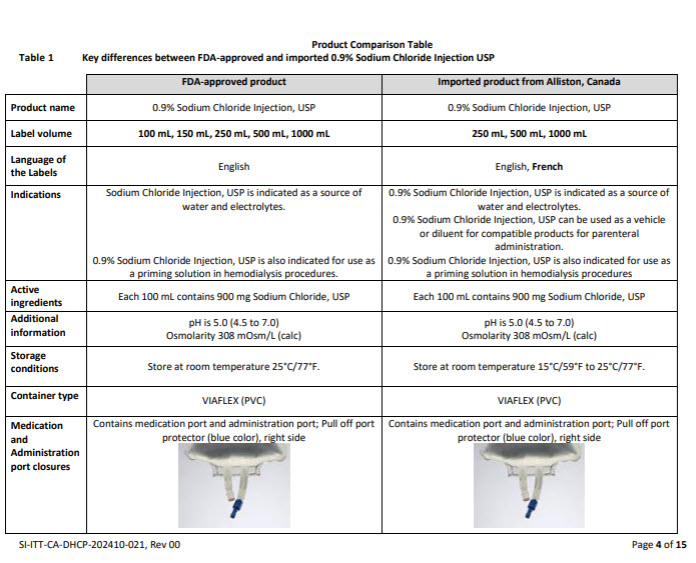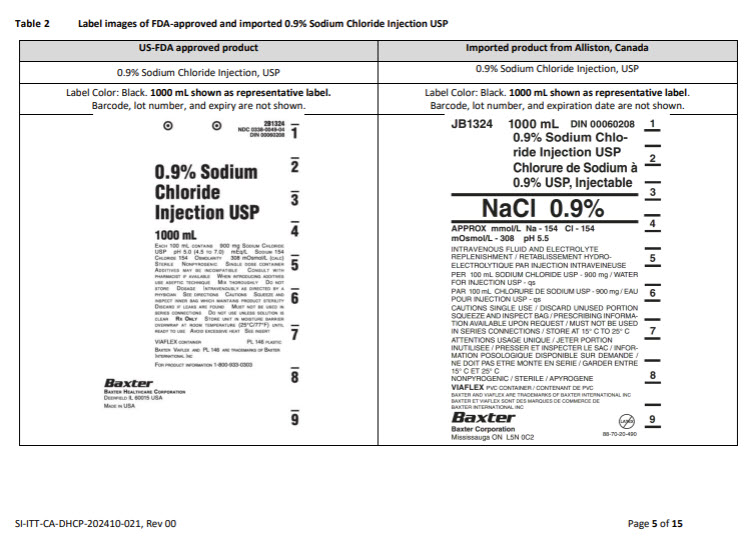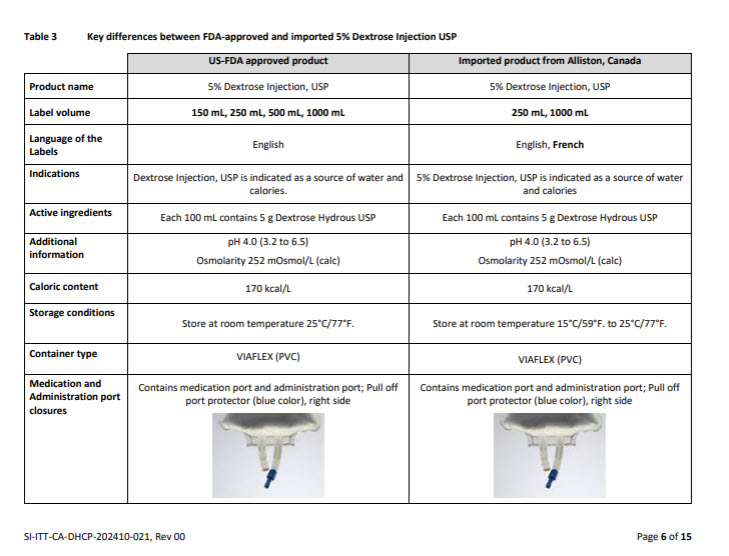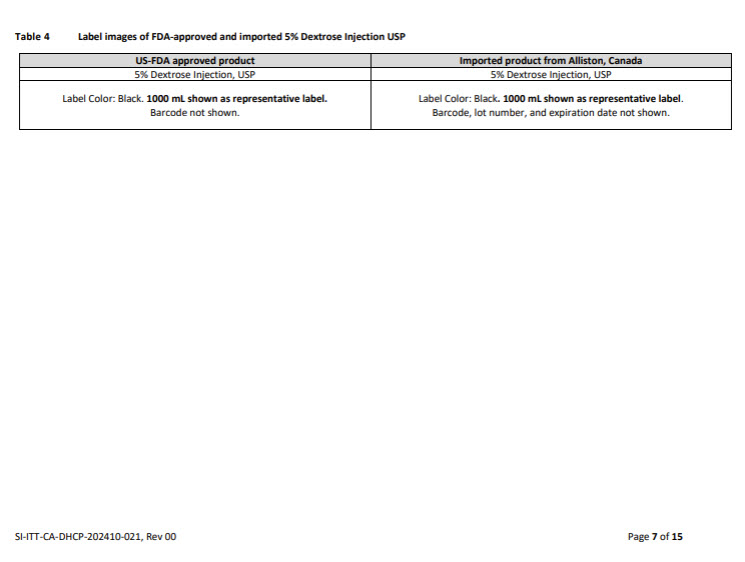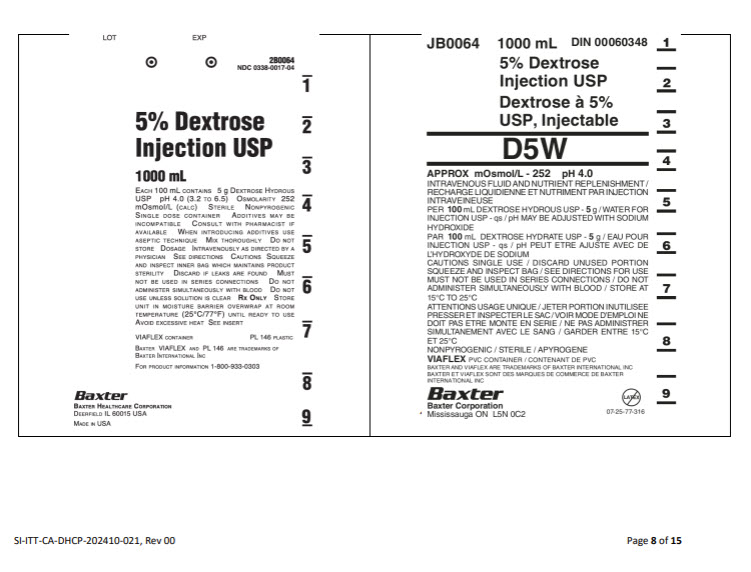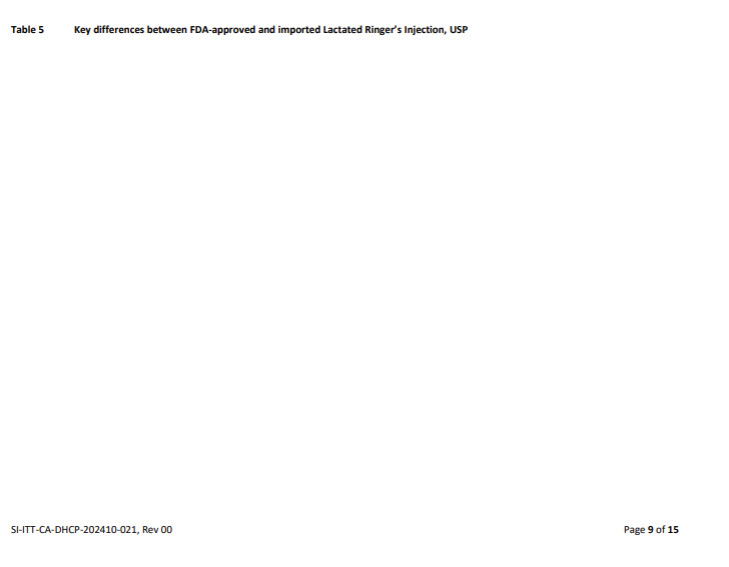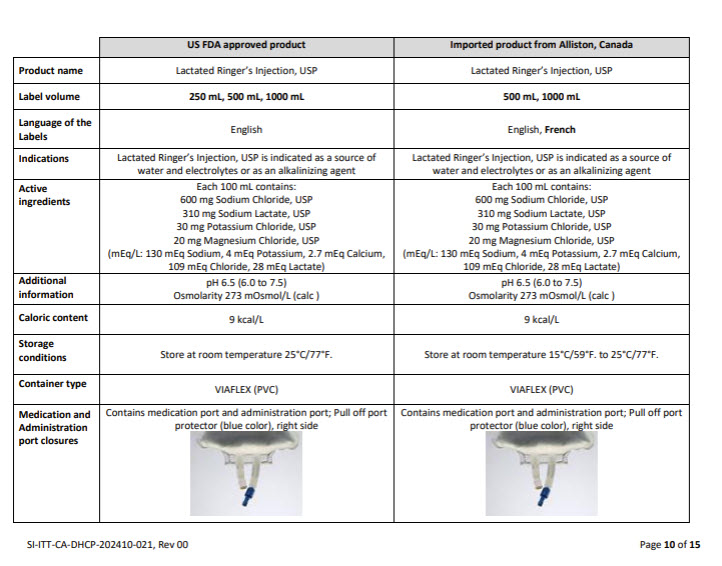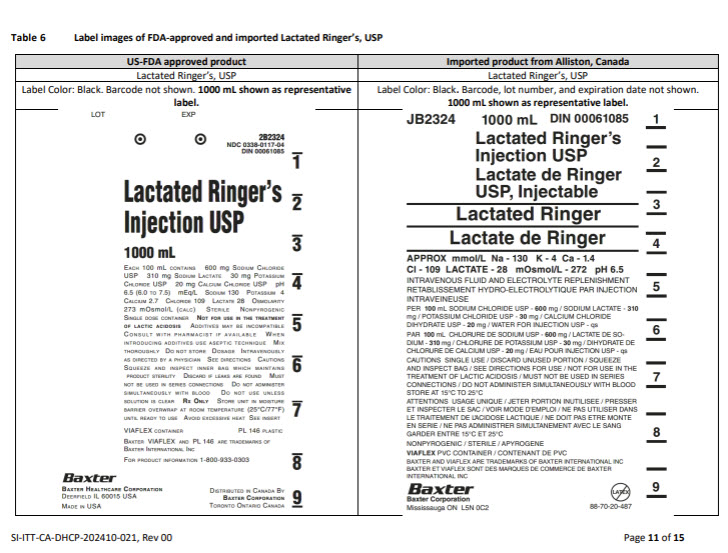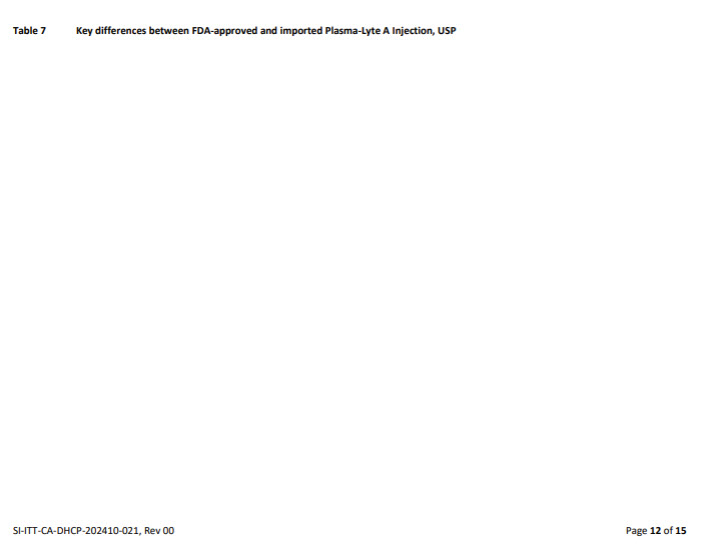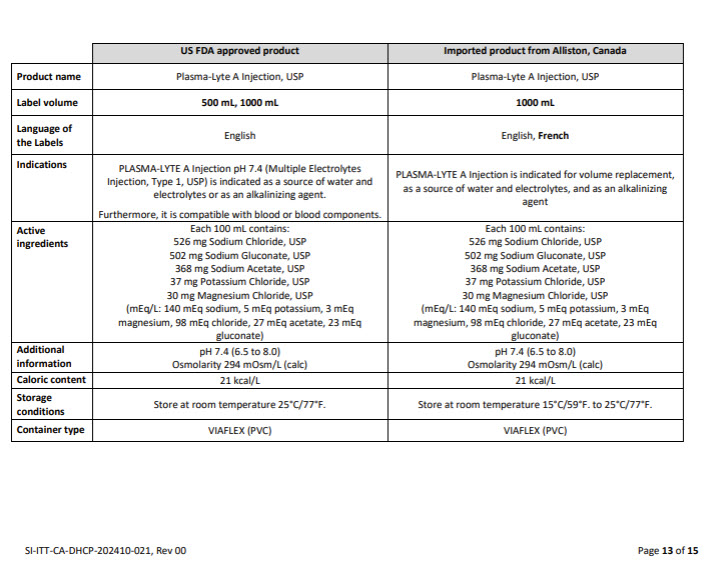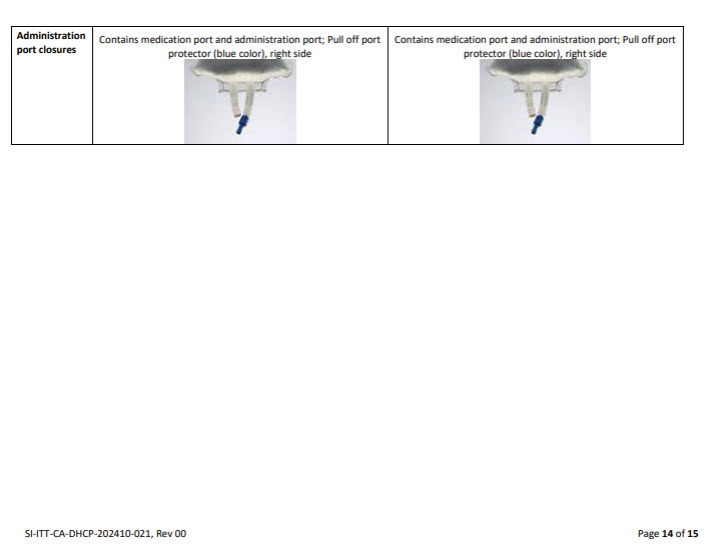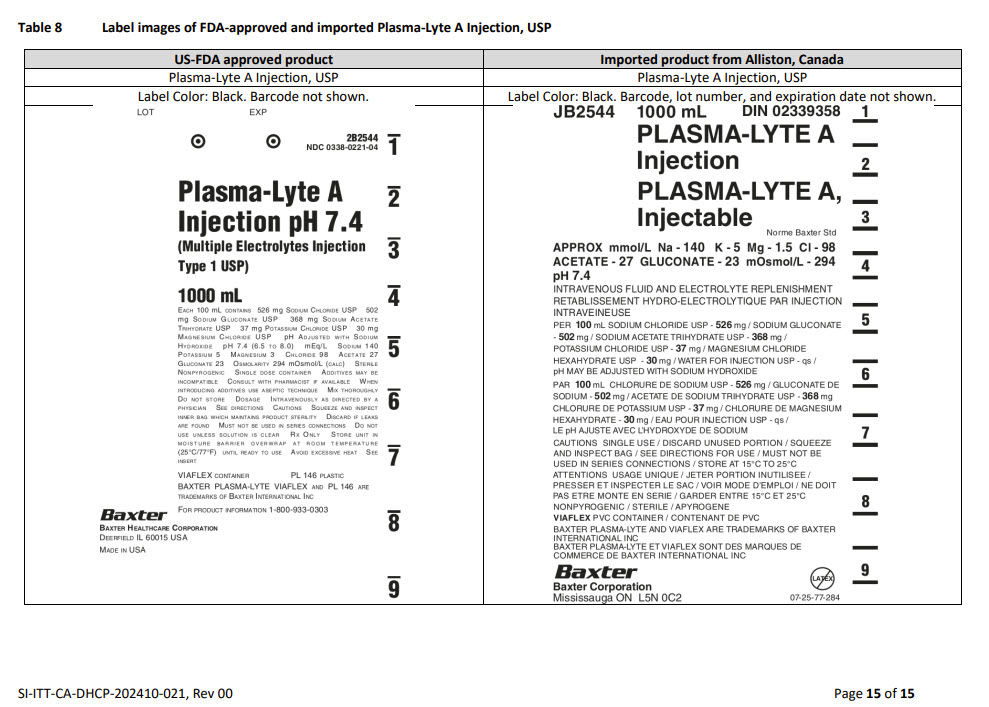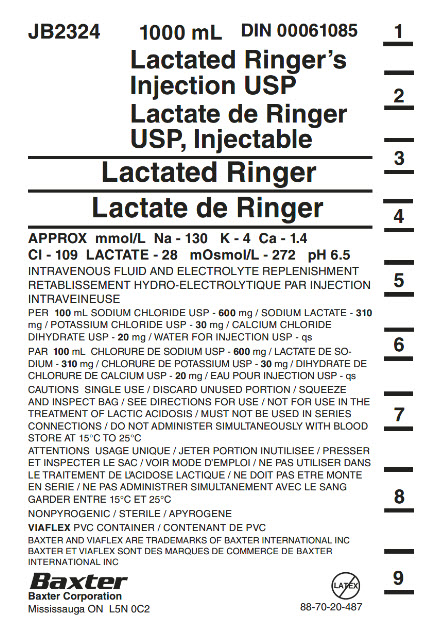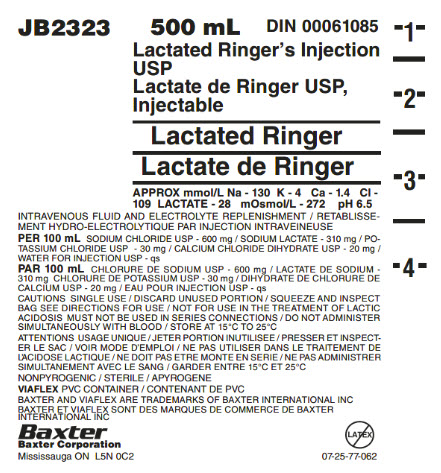 DRUG LABEL: Lactated Ringers
NDC: 0338-9600 | Form: INJECTION, SOLUTION
Manufacturer: Baxter Healthcare Company
Category: prescription | Type: HUMAN PRESCRIPTION DRUG LABEL
Date: 20241202

ACTIVE INGREDIENTS: SODIUM CHLORIDE 600 mg/100 mL; SODIUM LACTATE 310 mg/100 mL; POTASSIUM CHLORIDE 30 mg/100 mL; CALCIUM CHLORIDE 20 mg/100 mL
INACTIVE INGREDIENTS: WATER

Lactated ringer’s injection, usp in plastic container

Health Care Professional Letter

Reportin Adverse Events or Product Quality Issues

To report adverse events associated with these imported products, please call Baxter at 1-866-888-2472, or fax: 1-800-759-1801. Adverse events or quality problems experienced with the use of these imported products may also be reported to the FDA’s MedWatch Adverse Event Reporting program either online, or by regulary mail or by fax:

- Complete and submit the report Online: https://www.fda.gov/safety/medwatch-fda-safety-information-and-adverse-event-reporting-program
- Regular mail or Fax: Download form https://www.fda.gov/safety/medical-product-safety-information/medwatch-forms-fda-safety-reporting or call 1-800-332-1088 to request a reporting form, then complete and return to the address on the pre-addressed form, or submit by fax to 1-800-FDA-0178 (1-800-332-0178)

To report product quality issues associated with these imported products, please contact Baxter Product Surveillance through Baxter – Product Feedback Portal (https://productfeedback.baxter.com/).

Please refer to the FDA-approved prescribing information for each drug product as follows:

- 5% Dextrose Injection, USP (click DailyMed - DEXTROSE- dextrose monohydrate injection, solution)
- 0.9% Sodium Chloride Injection, USP (click DailyMed - SODIUM CHLORIDE injection, solution)
- Lactated Ringers Injection, USP (click DailyMed - LACTATED RINGERS- sodium chloride, potassium chloride, sodium lactate and calcium chloride injection, solution)

- Plasma-Lyte Injection, USP (click DailyMed - PLASMA-LYTE A- sodium chloride, sodium gluconate, sodium acetate, potassium chloride and magnesium chloride injection, solution)

PACKAGE/LABEL PRINCIPAL DISPLAY PANEL

Container Label

JB2324
1000 mL
DIN 00061085

Lactated Ringer’s
Injection USP

Lactate de Ringer
USP, Injectable

Lactated Ringer

Lactate de Ringer

APPROX mmol/L Na – 130 K – 4 Ca – 1.4
CI – 109 LACTATE – 28 mOsmol/L – 272 pH 6.5

INTRAVENOUS FLUID AND ELECTROLYTE REPLENISHMENT
RETABLISSEMENT HYDRO-ELECTROLYTIQUE PAR INJECTION
INTRAVENIEUSE

PER 100 mL SODIUM CHLORIDE USP – 600 mg / SODIUM LACTATE – 310
mg / POTASSIUM CHLORIDE USP – 30 mg / CALCIUM CHLORIDE
DIHYDRATE USP – 20 mg / WATER FOR INJECTION USP – qs

PAR 100 mL CHLORURE DE SODIUM USP – 600 mg / LACTATE DE SO-
DIUM – 310 mg/ CHLORURE DE POTASSIUM USP – 30 mg / DIHYDRATE DE
CHLORURE DE CALCIUM USP – 20 mg / EAU POUR INJECTION USP – qs

CAUTIONS SINGLE USE / DISCARD UNUSED PORTION / SQUEEZE
AND INSPECT BAG / SEE DIRECTIONS FOR USE / NOT FOR USE IN THE
TREATEMENT OF LACTIC ACIDOSIS / MUST NOT BE USED IN SERIES
CONNECTIONS / DO NOT ADMINSTER SIMULTANEOUSLY WITH BLOOD
STORE AT 15°C TO 25°C

ATTENTIONS USAGE UNIQUE / JETER PORTION INUTILISEE / PRESSER
ET INSPECTER LE SAC / VOIR MODE D’EMPLOI / NE PAS UTILISER DANS
LE TRAITEMENT DE L’ACIDOSE LACTIQUE / NE DOIT PAS ETRE MONTE
EN SERIE / NE PAS ADMINISTRER SIMULTANEMENT AVEC LE SANG
GARDER ENTRE 15°C ET 25°C

NONPYROGENIC / STERILE / APYROGENE

VIAFLEX PVC CONTAINER / CONTENANT DE PVC

BAXTER AND VIAFLEX ARE TRADEMARKS OF BAXTER INTERNATIONAL INC
BAXTER ET VIAFLEX SONT DES MARQUES DE COMMERCE DE BAXTER
INTERNATIONAL INC

Baxter Logo
Baxter Corporation
Mississauga ON L5N 0C2

No Latex Label

88-70-20-487

1

_

2

_

3

_

4

_

5

_

6

_

7

_

8

_

9

Container Label

JB2323
500 mL
DIN 00061085

Lactated Ringer’s Injection
USP

Lactate de Ringer USP,
Injectable

Lactated Ringer

Lactate de Ringer

APPROX mmol/L Na – 130 K – 4 Ca – 1.4 CI
109 LACTATE – 28 mOsmol/L – 272 pH 6.5

INTRAVENOUS FLUID AND ELECTROLYTE REPLENISHMENT / RETABLISSE-
MENT HYDRO-ELECTROLYTIQUE PAR INJECTION INTRAVENIEUSE

PER 100 mL SODIUM CHLORIDE USP – 600mg / SODIUM LACTATE – 310mb / PO-
TASSIUM CHLORIDE USP – 30mg / CALCIUM CHLORIDE DIHYDRATE USP – 20mg /
WATER FOR INJECTION USP – qs

PAR 100 mL CHLORURE DE SODIUM USP – 600mg / LACTATE DE SODIUM –
310mg/ CHLORURE DE POTASSIUM USP – 30mg / DIHYDRATE DECHLORURE DE
CALCIUM USP – 20mg / EAU POUR INJECTION USP – qs

CAUTIONS SINGLE USE / DISCARD UNUSED PORTION / SQUEEZE AND INSPECT
BAG / SEE DIRECTIONS FOR USE / NOT FOR USE IN THE TREATEMENT OF LACTIC
ACIDOSIS / MUST NOT BE USED IN SERIES CONNECTIONS / DO NOT ADMINSTER
SIMULTANEOUSLY WITH BLOOD STORE AT 15°C TO 25°C

ATTENTIONS USAGE UNIQUE / JETER PORTION INUTILISEE / PRESSER ET INSPECT-
ER LE SAC / VOIR MODE D’EMPLOI / NE PAS UTILISER DANS LE TRAITEMENT DE
L’ACIDOSE LACTIQUE / NE DOIT PAS ETRE MONTE EN SERIE / NE PAS ADMINISTRER
SIMULTANEMENT AVEC LE SANG GARDER ENTRE 15°C ET 25°C

NONPYROGENIC / STERILE / APYROGENE

VIAFLEX PVC CONTAINER / CONTENANT DE PVC

BAXTER AND VIAFLEX ARE TRADEMARKS OF BAXTER INTERNATIONAL INC
BAXTER ET VIAFLEX SONT DES MARQUES DE COMMERCE DE BAXTER
INTERNATIONAL INC

Baxter Logo
Baxter Corporation
Mississauga ON L5N 0C2

No Latex Label

07-25-77-062

-1-

_

-2-

_

-3-

_

-4-